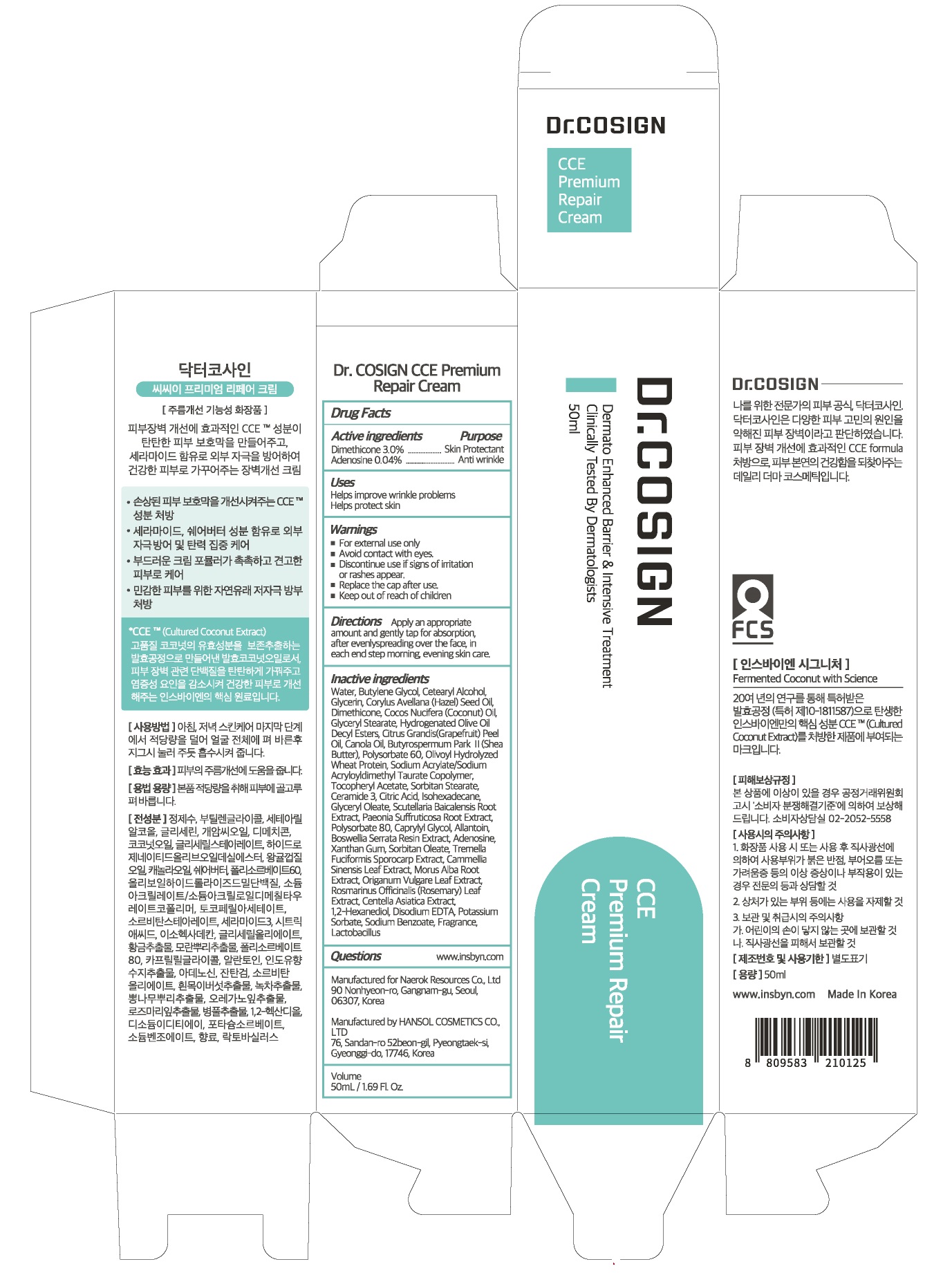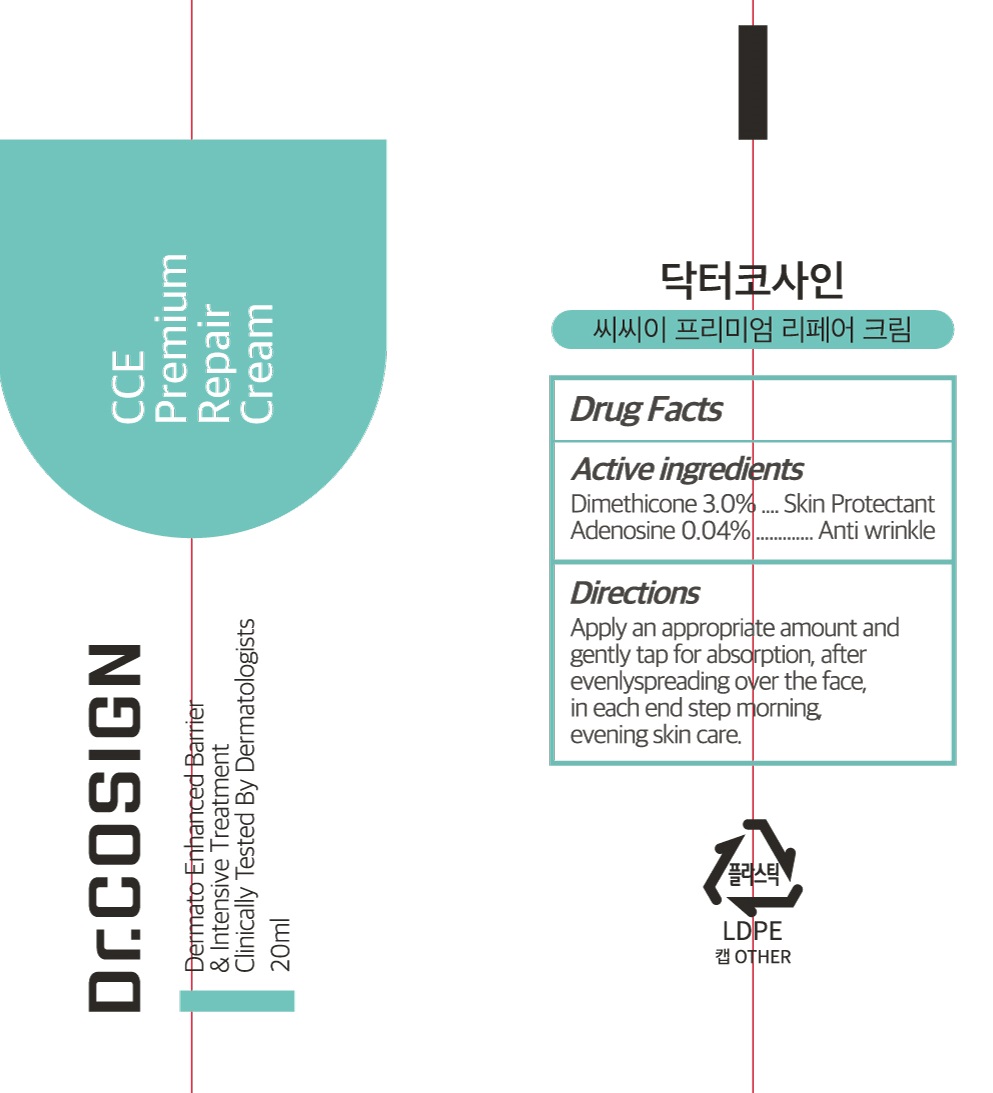 DRUG LABEL: Dr COSIGN CCE Premium Repair
NDC: 72642-020 | Form: CREAM
Manufacturer: Naerok Resources Co., Ltd
Category: otc | Type: HUMAN OTC DRUG LABEL
Date: 20181106

ACTIVE INGREDIENTS: Dimethicone 3.0 g/100 mL; Adenosine 0.04 g/100 mL
INACTIVE INGREDIENTS: Water; Butylene Glycol

ACTIVE INGREDIENT

Active ingredients: Dimethicone 3.0%, Adenosine 0.04%

INACTIVE INGREDIENT

Inactive ingredients:

Water, Butylene Glycol, Cetearyl Alcohol, Glycerin, Corylus Avellana (Hazel) Seed Oil, Cocos Nucifera (Coconut) Oil, Glyceryl Stearate, Hydrogenated Olive Oil Decyl Esters, Citrus Grandis(Grapefruit) Peel Oil, Canola Oil,
Butyrospermum Park Ⅱ(Shea Butter), Polysorbate 60, Olivoyl Hydrolyzed Wheat Protein, Sodium Acrylate/Sodium Acryloyldimethyl Taurate Copolymer, Tocopheryl Acetate, Sorbitan Stearate, Ceramide 3, Citric Acid, Isohexadecane, Glyceryl Oleate, Scutellaria Baicalensis Root Extract, Paeonia Suffruticosa Root Extract, Polysorbate 80, Caprylyl Glycol, Allantoin, Boswellia Serrata Resin Extract, Xanthan Gum, Sorbitan Oleate, Tremella Fuciformis Sporocarp Extract, Cammellia Sinensis Leaf Extract, Morus Alba Root Extract, Origanum Vulgare Leaf Extract, Rosmarinus Officinalis (Rosemary) Leaf Extract, Centella Asiatica Extract, 1,2-Hexanediol, Disodium EDTA, Potassium Sorbate, Sodium Benzoate, Fragrance, Lactobacillus

PURPOSE

Purpose: Skin Protectant, Anti wrinkle

WARNINGS

For external use only

Avoid contact with eyes.

Discontinue use if signs of irritation or rashes appear.

Replace the cap after use.

Keep out of reach of children

KEEP OUT OF REACH OF CHILDREN

Uses

Helps improve wrinkle problems

Helps protect skin

Directions

Apply an appropriate amount and gently tap for absorption, after evenly spreading over the face, in each end step morning, evening skin care.